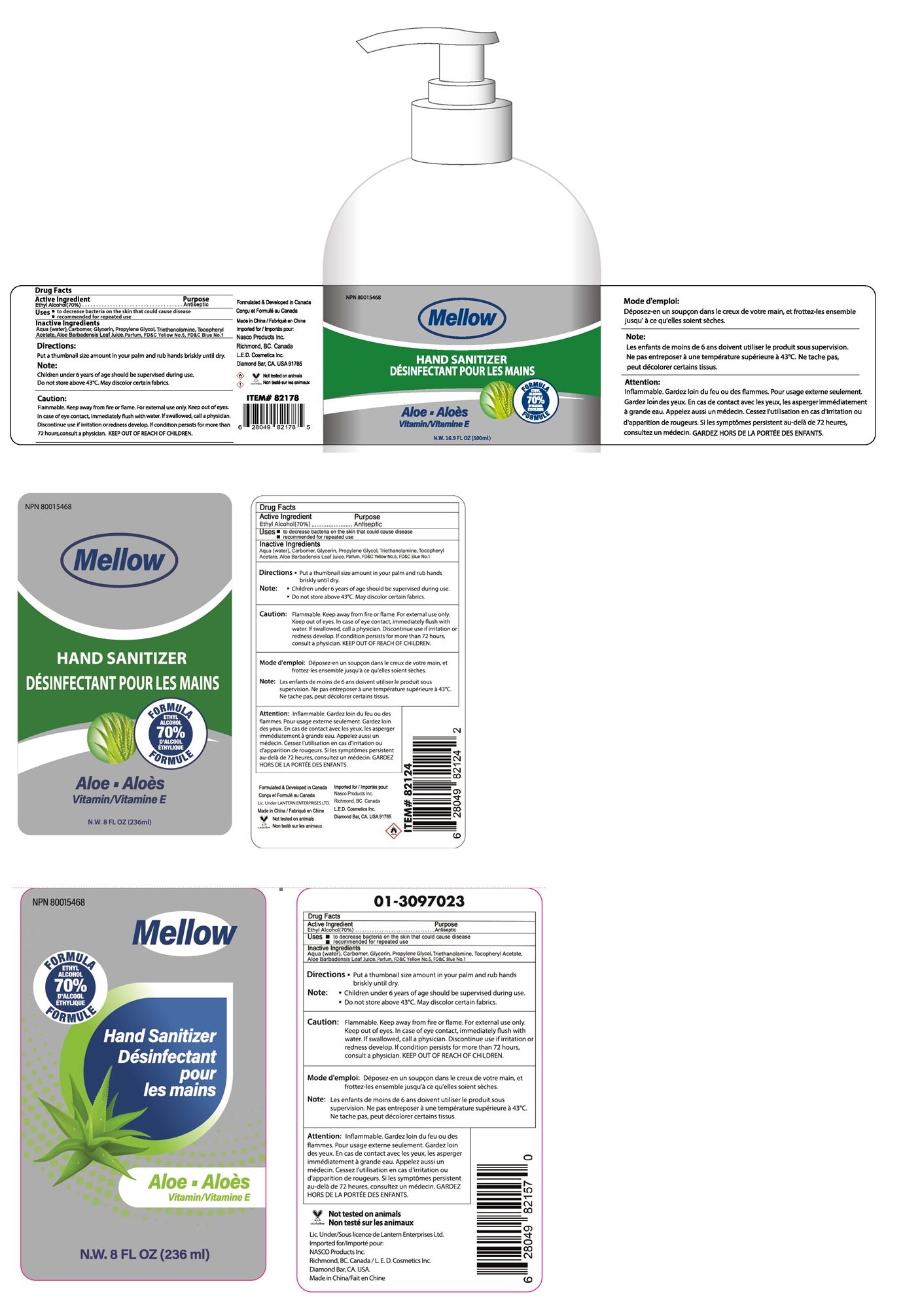 DRUG LABEL: MELLOW HAND SANITIZER ALOE
NDC: 77725-005 | Form: LIQUID
Manufacturer: L.e.d. Cosmetics, Inc.
Category: otc | Type: HUMAN OTC DRUG LABEL
Date: 20241210

ACTIVE INGREDIENTS: ALCOHOL 70 mL/100 mL
INACTIVE INGREDIENTS: WATER; CARBOMER HOMOPOLYMER, UNSPECIFIED TYPE; GLYCERIN; PROPYLENE GLYCOL; TROLAMINE; .ALPHA.-TOCOPHEROL ACETATE; ALOE VERA LEAF; FD&C YELLOW NO. 5; FD&C BLUE NO. 1

MELLOW HAND SANITIZER

Active Ingredient

Ethyl Alcohol(70%)

Purpose

Antiseptic

INDICATIONS AND USAGE

Uses • to decrease bacteria on the skin that could disease

• recommended for repeated use

Inactive Ingredients

Aqua (water), Carbomer, Glycerin, Propylene Glycol, Triethanolamine, Tocopheryl Acetate, Aloe Barbadensis Leaf Juice, Parfum, FD&C Yellow No.5, FD&C Blue No.1

DOSAGE AND ADMINISTRATION

Directions • Put a thumbnail size amount in your palm and rub hands briskly until dry.

Note : • Children under 6 years of age should be supervised during use.

STORAGE AND HANDLING

• Do not store above 43˚C. May discolor certain fabrics.

WARNINGS

Caution: Flammable. Keep away from fire or flame. For external use only. Keep out of eyes. In case of eye contact, immediately flush with water.

If swallowed, call a physician. Discontinue use if irritation or redness develop. If condition persists for more than 72 hours, consult a physician.

KEEP OUT OF REACH OF CHILDREN.

FORMULA

ETHYL ALCOHOL 70%

Aloe

Vitamin E

Formulated & Developed in Canada

Made in China

Lic.Under Lantern Enterprises Ltd.

Imported for:

Nasco Products Inc.

Richmond, BC. Canada

L.E.D. Cosmetics Inc.

Diamond Bar, CA. USA 91765

Not tested on animals